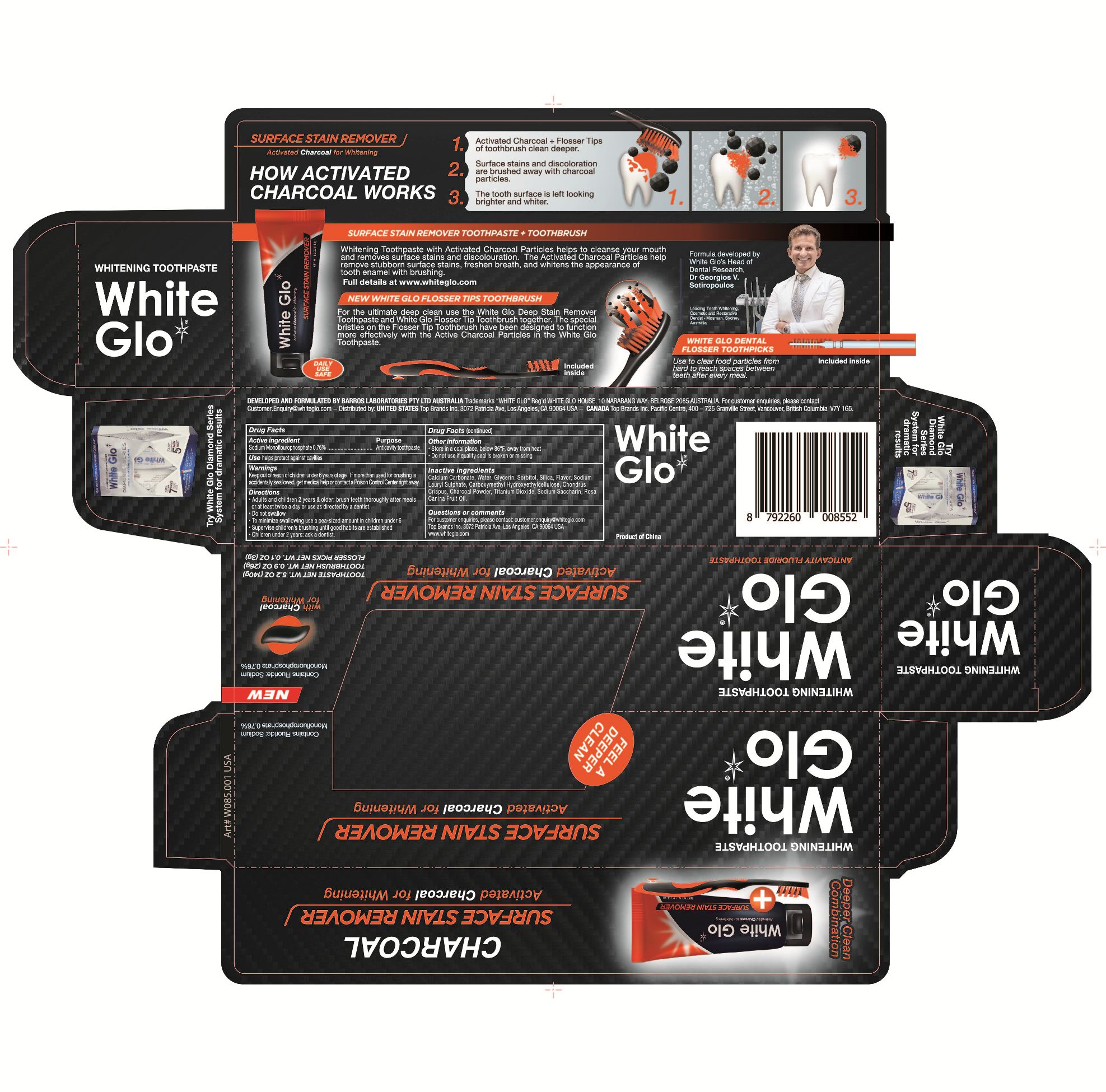 DRUG LABEL: White-Glo whiting tooth
NDC: 71167-004 | Form: PASTE
Manufacturer: HUAIAN ZONGHENG BIO-TECH CO., LTD
Category: otc | Type: HUMAN OTC DRUG LABEL
Date: 20180202

ACTIVE INGREDIENTS: SODIUM MONOFLUOROPHOSPHATE 0.76 g/100 g
INACTIVE INGREDIENTS: CHONDRUS CRISPUS; CALCIUM CARBONATE; WATER; GLYCERIN; TITANIUM DIOXIDE; SORBITOL; SODIUM SILICATE; SODIUM LAURYL SULFATE; CARBOXYMETHYLCELLULOSE; POTASSIUM SODIUM SACCHARATE; ROSA CANINA FLOWER OIL

71167-004

Active Ingredient

sodium monofluorphosphate 0.76%

Purpose

Anticavitytoothpaste

Use

helps protect against cavities

Warning

Keep out of reach of children under 6 years of age.
If more than used for brushing is accidently swallowed get medical help or contact a poison control center right away.

Directions

Adults and children 6 years of age and older:brush teeth thoroughly, after meals or at least twice a day or use as directed by a dentist.

do not swallow

to minimize swallowing use a pea-sized amount in children under 6

supervise children's burshing ntil good habits are established

children under 2 years ask a dentist

Inactive Ingredients

Calcium Carbonate,Aqua,Glycerin,Sorbitol,Silica,Aroma,Sodium Lauryl Sulphate,Carboxymethyl Hydroxyethyl cellulose,Chondrus Crispus,CI77891(Titanium Dioxide),Sodium saccharin,rose canina fruit oil

Keep out of reach of children under 6 years of age